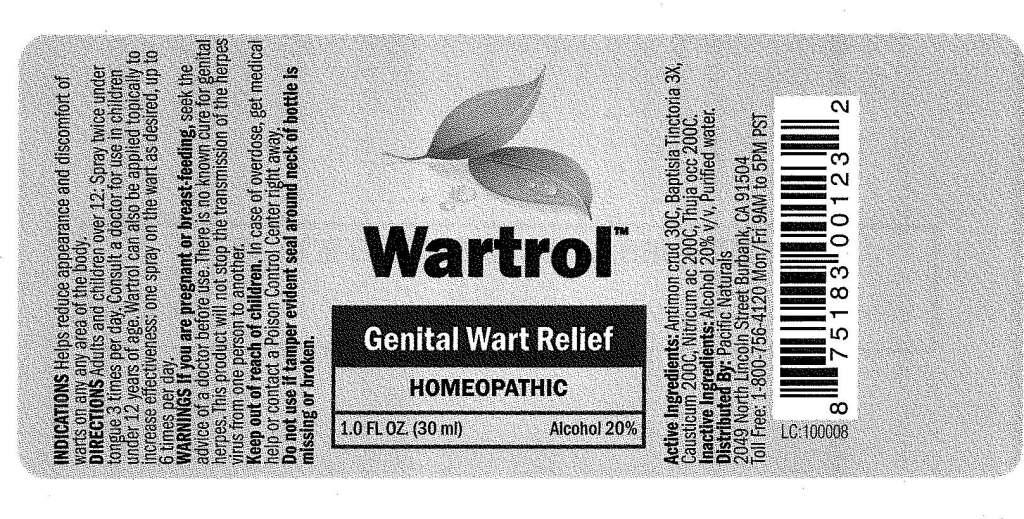 DRUG LABEL: Wartrol
NDC: 50845-0003 | Form: SPRAY
Manufacturer: Liddell Laboratories
Category: homeopathic | Type: HUMAN OTC DRUG LABEL
Date: 20100916

ACTIVE INGREDIENTS: ANTIMONY TRISULFIDE 30 [hp_C]/1 mL; BAPTISIA TINCTORIA ROOT 3 [hp_X]/1 mL; CAUSTICUM 200 [hp_C]/1 mL; NITRIC ACID 200 [hp_C]/1 mL; THUJA OCCIDENTALIS LEAFY TWIG 200 [hp_C]/1 mL
INACTIVE INGREDIENTS: WATER; ALCOHOL

Wartrol

ACTIVE INGREDIENT

ACTIVE INGREDIENTS: Antimonium crudum 30C, Baptisia tinctoria 3X, Causticum 200C, Nitricum acidum 200C, Thuja occidentalis 200C.

PURPOSE

INDICATIONS: Help reduce appearance and discomfort of warts on any area of the body.

WARNINGS

WARNINGS: If you are pregnant or breast-feeding, seek the advice of a doctor before use. There is no known cure for genital herpes. This product will not stop the transmission of the herpes virus from one person to another.

Keep out of reach of children. In case of overdose, get medical help or contact a Poison Control Center right away.

Do not use if tamper evident seal around neck of bottle is missing or broken.

DOSAGE AND ADMINISTRATION

DIRECTIONS: Adults and children over 12: Spray twice under tongue 3 times per day. Consult a doctor for use in children under 12 years of age. Wartrol can also be applied topically to increase effectiveness: one spray on the wart as desired, up to 6 times per day.

INACTIVE INGREDIENTS: Alcohol 20% v/v, Purified water.

KEEP OUT OF REACH OF CHILDREN: In case of overdose, get medical help or contact a Poison Control Center right away.

INDICATIONS AND USAGE

INDICATIONS: Helps reduce appearance and discomfort of warts on any area of the body.

QUESTIONS

Distributed By:

Pacific Naturals

2049 North Lincoln Street

Burbank, CA 91540

Toll Free: 1-800-4120 Mon/Fri 9AM to 5PM PST

PACKAGE LABEL

Wartrol

Genital Wart Relief

HOMEOPATHIC

1.0 FL. OZ. (30 ml)